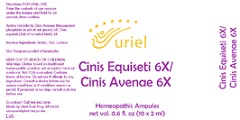 DRUG LABEL: Cinis Equiseti 6X Cinis Avenae 6X
NDC: 48951-3243 | Form: LIQUID
Manufacturer: Uriel Pharmacy Inc.
Category: homeopathic | Type: HUMAN OTC DRUG LABEL
Date: 20210309

ACTIVE INGREDIENTS: MAGNESIUM PHOSPHATE, TRIBASIC, PENTAHYDRATE 6 [hp_X]/1 mL; EQUISETUM ARVENSE TOP 6 [hp_X]/1 mL
INACTIVE INGREDIENTS: WATER; SODIUM CHLORIDE; LACTOSE, UNSPECIFIED FORM

Cinis Equiseti 6X Cinis Avenae 6X

INDICATIONS AND USAGE

Directions: FOR ORAL USE.

DOSAGE AND ADMINISTRATION

Take the contents of one ampule under the tongue and hold for 30 seconds, then swallow.

ACTIVE INGREDIENT

Active Ingredients: Cinis Avenae (Magnesium phosphate in ash of oat grains) 6X, Cinis equiseti (Ash of horsetail herb) 6X

Inactive Ingredients: Water, Salt, Lactose

PURPOSE

Use: Temporary relief of headache.

KEEP OUT OF REACH OF CHILDREN.

WARNINGS

Warnings: Claims based on traditional homeopathic practice, not accepted medical evidence. Not FDA evaluated. Contains traces of lactose. Do not use if allergic to any ingredient. Consult a doctor before use for serious conditions or if conditions worsen or persist. If pregnant or nursing, consult a doctor before use.

Questions? Call 866.642.2858
Made by Uriel, East Troy, WI 53120
www.urielpharmacy.com Lot: